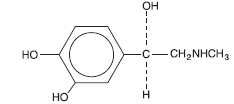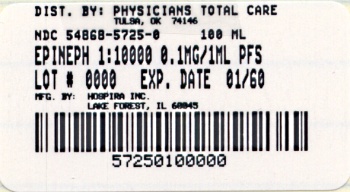 DRUG LABEL: EPINEPHRINE
NDC: 54868-5725 | Form: INJECTION, SOLUTION
Manufacturer: Physicians Total Care, Inc.
Category: prescription | Type: HUMAN PRESCRIPTION DRUG LABEL
Date: 20100503

ACTIVE INGREDIENTS: EPINEPHRINE 0.1 mg/1 mL
INACTIVE INGREDIENTS: SODIUM CHLORIDE; SODIUM METABISULFITE; CITRIC ACID MONOHYDRATE; SODIUM CITRATE

Epinephrine Injection, USP
1:10,000
1 mg (0.1 mg/mL)
Abboject® Syringe

Rx Only
Revised: 10/2004

Protect solution from light; do not use the Injection if its color is pinkish or darker than slightly yellow or if it containsa precipitate

DESCRIPTION

Epinephrine Injection, USP is a sterile, nonpyrogenic solution administered parenterally by the intravenous or intracardiac (left ventricular chamber) routes, or via endotracheal tube into the bronchial tree.

Each milliliter (mL) of the 1:10,000 solution contains epinephrine 0.1 mg; sodium chloride 8.16 mg; sodium metabisulfite added 0.46 mg; citric acid, anhydrous 2 mg and sodium citrate, dihydrate 0.6 mg added as buffers. May contain additional citric acid and/or sodium citrate for pH adjustment. pH 3.3 (2.2 to 5.0). Epinephrine Injection, USP is oxygen sensitive.

The solution contains no bacteriostat or antimicrobial agent and is intended for use only as a single-dose injection. When smaller doses are required the unused portion should be discarded.

Epinephrine Injection, USP is a parenteral adrenergic (sympathomimetic) agent and cardiac stimulant.

The drug belongs to the group of endogenous compounds known as catecholamines.

Sodium Chloride, USP is chemically designated NaCl, a white crystalline powder freely soluble in water.

Epinephrine, USP is chemically designated 4-[1-hydroxy-2-(methylamino) ethyl]-1, 2 benzenediol, a white, microcrystalline powder. With acids, it forms salts that are freely soluble in water. Epinephrine has the following structural formula:

CLINICAL PHARMACOLOGY

The actions of epinephrine resemble the effects of stimulation of adrenergic nerves. To a variable degree it acts on both alpha and beta receptor sites of sympathetic effector cells. Its most prominent actions are on the beta receptors of the heart, vascular and other smooth muscle. When given by rapid intravenous injection, it produces a rapid rise in blood pressure, mainly systolic, by (1) direct stimulation of cardiac muscle which increases the strength of ventricular contraction, (2) increasing the heart rate and (3) constriction of the arterioles in the skin, mucosa and splanchnic areas of the circulation.

When given by slow intravenous injection, epinephrine usually produces only a moderate rise in systolic and a fall in diastolic pressure. Although some increase in pulse pressure occurs, there is usually no great elevation in mean blood pressure. Accordingly, the compensatory reflex mechanisms that come into play with a pronounced increase in blood pressure do not antagonize the direct cardiac actions of epinephrine as much as with catecholamines that have a predominant action on alpha receptors.

Total peripheral resistance decreases by action of epinephrine on beta receptors of the skeletal muscle vasculature and blood flow is thereby enhanced. Usually this vasodilator effect of the drug on the circulation predominates so that the modest rise in systolic pressure which follows slow injection or absorption is mainly the result of direct cardiac stimulation and increase in cardiac output. In some instances peripheral resistance is not altered or may even rise owing to a greater ratio of alpha to beta activity in different vascular areas.

Epinephrine relaxes the smooth muscles of the bronchi and iris and is a physiologic antagonist of histamine. The drug also produces an increase in blood sugar and glycogenolysis in the liver.

Intravenous injection produces an immediate and intensified response. Following intravenous injection epinephrine disappears rapidly from the blood stream. Epinephrine is rapidly inactivated in the body and is degraded by enzymes in the liver and other tissues. The larger portion of injected doses is excreted in the urine as inactivated compounds and the remainder either partly unchanged or conjugated.

The drug becomes fixed in the tissues and is inactivated chiefly by enzymatic transformation to metanephrine or normetanephrine either of which is subsequently conjugated and excreted in the urine in the form of sulfates and glucuronides. Either sequence results in the formation of 3-methoxy-4-hydroxy-mandelic acid (vanillyl-mandelic acid: VMA) which also is detectable in the urine.

Sodium chloride added to render the solution isotonic for injection of the active ingredient is present in amounts insufficient to affect serum electrolyte balance of sodium (Na+) and chloride (Cl–) ions.

INDICATIONS AND USAGE

Epinephrine Injection, USP is indicated for intravenous injection in (1) treatment of acute hypersensitivity (anaphylactoid reactions to drugs, animal serums and other allergens), (2) treatment of acute asthmatic attacks to relieve bronchospasm not controlled by inhalation or subcutaneous administration of other solutions of the drug and (3) treatment and prophylaxis of cardiac arrest and attacks of transitory atrioventricular (A-V) heart block with syncopal seizures (Stokes-Adams Syndrome).

In acute attacks of ventricular standstill, physical measures should be applied first. When external cardiac compression and attempts to restore the circulation by electrical defibrillation or use of a pacemaker fail, intracardiac puncture and intramyocardial injection of epinephrine may be effective.

CONTRAINDICATIONS

Epinephrine is contraindicated in patients with known hypersensitivity to sympathomimetic amines, in patients with angle closure glaucoma, and patients in shock (nonanaphylactic). It should not be used in patients anesthetized with agents such as cyclopropane or halothane as these may sensitize the heart to arrhythmic action of sympathomimetic drugs.

Epinephrine should not ordinarily be used in those cases where vasopressor drugs may be contraindicated, e.g., in thyrotoxicosis, diabetes, in obstetrics when maternal blood pressure is in excess of 130/80 and in hypertension and other cardiovascular disorders.

WARNINGS

Inadvertently induced high arterial blood pressure may result in angina pectoris, aortic rupture or cerebral hemorrhage.

Epinephrine may induce potentially serious cardiac arrhythmias in patients not suffering from heart disease and patients with organic heart disease or who are receiving drugs that sensitize the myocardium.

Parenterally administered epinephrine initially may produce constriction of renal blood vessels and decrease urine formation.

Epinephrine is the preferred treatment for serious allergic or other emergency situations even though this product contains sodium metabisulfite, a sulfite that may in other products cause allergic-type reactions including anaphylactic symptoms or life-threatening or less severe asthmatic episodes in certain susceptible persons. The alternatives to using epinephrine in a life-threatening situation may not be satisfactory. The presence of a sulfite(s) in this product should not deter administration of the drug for treatment of serious allergic or other emergency situations.

PRECAUTIONS

The solution should be protected from light. Do not use the injection if its color is pinkish or darker than slightly yellow or if it contains a precipitate.

Do not administer unless solution is clear and seal is intact. Discard unused portion.

Although epinephrine can produce ventricular fibrillation, its actions in restoring electrical activity in asystole and in enhancing defibrillation of the fibrillating ventricle are well documented. The drug, however, should be used with caution in patients with ventricular fibrillation.

In patients with prefibrillatory rhythm, intravenous epinephrine must be used judiciously with extreme caution because of its excitatory action on the heart. Since the myocardium is sensitized to this action of the drug by many anesthetic agents, epinephrine may convert asystole to ventricular fibrillation if used in the treatment of anesthetic cardiac accidents.

Epinephrine should be used cautiously in patients with hyperthyroidism, hypertension and cardiac arrhythmias. All vasopressors should be used cautiously in patients taking monoamine oxidase (MAO) inhibitors.

Epinephrine should not be administered concomitantly with other sympathomimetic drugs (such as isoproterenol) because of possible additive effects and increased toxicity. Combined effects may induce serious cardiac arrhythmias. They may be administered alternately when the preceding effect of other such drug has subsided.

Administration of epinephrine to patients receiving cyclopropane or halogenated hydrocarbon general anesthetics such as halothane which sensitize the myocardium, may induce cardiac arrhythmia. (See CONTRAINDICATIONS). When encountered, such arrhythmias may respond to administration of a beta-adrenergic blocking drug. Epinephrine also should be used cautiously with other drugs (e.g., digitalis, glycosides) that sensitize the myocardium to the actions of sympathomimetic drugs.

Diuretic agents may decrease vascular response to pressor drugs such as epinephrine.

Epinephrine may antagonize the neuron blockade produced by guanethidine resulting in decreased antihypertensive effect and requiring increased dosage of the latter.

Pregnancy Category C

Animal reproduction studies have not been conducted with epinephrine. It is also not known whether epinephrine can cause fetal harm when administered to a pregnant woman or can affect reproduction capacity. Epinephrine should be given to a pregnant woman only if clearly needed.

Labor and Delivery

Parenteral administration of epinephrine if used to support blood pressure during low or other spinal anesthesia for delivery can cause acceleration of fetal heart rate and should not be used in obstetrics when maternal blood pressure exceeds 130/80. (See CONTRAINDICATIONS).

ADVERSE REACTIONS

Transient and minor side effects of anxiety, headache, fear and palpitations occur with systemic therapeutic doses, especially in hyperthyroid individuals. Adverse effects such as cardiac arrhythmias and excessive rise in blood pressure may also occur with therapeutic doses or inadvertent overdosage. Other adverse reactions include cerebral hemorrhage, hemiplegia, subarachnoid hemorrhage, anginal pain in patients with angina pectoris, anxiety, restlessness, throbbing headache, tremor, weakness, dizziness, pallor and respiratory difficulty.

OVERDOSAGE

Erroneous administration of large doses of epinephrine may lead to precordial distress, vomiting, headache, dyspnea, as well as unusually elevated blood pressure. (See WARNINGS.) Toxic effects of overdosage can be counteracted by injection of an alpha-adrenergic blocker and a beta- adrenergic blocker. In the event of a sharp rise in blood pressure, rapid-acting vasodilators such as the nitrites, or alpha-adrenergic blocking agents can be given to counteract the marked pressor effect of large doses of epinephrine.

DOSAGE AND ADMINISTRATION

Epinephrine Injection, USP is administered by intravenous injection and/or in cardiac arrest, by intracardiac injection into the left ventricular chamber or via endotracheal tube directly into the bronchial tree. The adult intravenous dose for hypersensitivity reactions or to relieve bronchospasm usually ranges from 0.1 to 0.25 mg (1 to 2.5 mL of 1:10,000 solution), injected slowly. Neonates may be given a dose of 0.01 mg per kg of body weight; for the infant 0.05 mg is an adequate initial dose and this may be repeated at 20 to 30 minute intervals in the management of asthma attacks.

In cardiac arrest, 0.5 to 1.0 mg (5 to 10 mL of 1:10,000 solution) may be given. During a resuscitation effort, 0.5 mg (5 mL) should be administered intravenously every five minutes.

Intracardiac injection should only be administered by personnel well trained in the technique, if there has not been sufficient time to establish an intravenous route. The intracardiac dose usually ranges from 0.3 to 0.5 mg (3 to 5 mL of 1:10,000 solution).

Alternatively, if the patient has been intubated, epinephrine can be injected via the endotracheal tube directly into the bronchial tree at the same dosage as for intravenous injection. It is rapidly absorbed through the lung capillary bed.

Parenteral drug products should be inspected visually for particulate matter and discoloration prior to administration, whenever solution and container permit. (See PRECAUTIONS.)

To prevent needle-stick injuries, needles should not be recapped, purposely bent or broken by hand.

HOW SUPPLIED

Epinephrine Injection, USP 1:10,000 1 MG (0.1 mg/mL) is supplied as:

10 x 10 mL syringe | NDC 54868-5725-0

STORAGE AND HANDLING

Store at 20 to 25°C (68 to 77°F). [See USP Controlled Room Temperature.]

Protect from light.

TO PREVENT NEEDLE-STICK INJURIES, NEEDLES SHOULD NOT BE RECAPPED, PURPOSELY BENT OR BROKEN BY HAND.

Manufactured By:
Hospira, Inc.,
Lake Forest, IL 60045 USA

Abboject® is a trademark of the Abbott group of companies.

Relabeling of "Additional" barcode label by:
Physicians Total Care, Inc.
Tulsa, OK 74146

PRINCIPAL DISPLAY PANEL

NDC 54868-5725-0

10 mL

Epinephrine
Injection, USP
1:10,000
1 mg (0.1 mg/mL)

Rx Only

Each mL Contains:
epinephrine 0.1 mg; sodium chloride 8.16 mg; sodium metabisulfite added 0.46 mg and citric acid, anhydrous 2 mg and sodium citrate, dihydrate 0.6 mg added as buffers. May contain additional citric acid and/or sodium citrate for pH adjustment.

Usual dosage: See insert

PROTECT FROM LIGHT.

Store at 20°-25°C (68° -77°F) (See USP Controlled Room Temperature).

Keep this and all medications out of the reach of children.